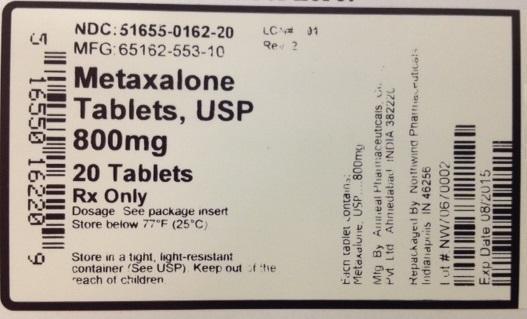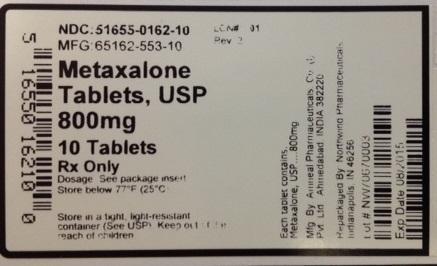 DRUG LABEL: Metaxalone
NDC: 51655-162 | Form: TABLET
Manufacturer: Northwind Pharmaceuticals
Category: prescription | Type: HUMAN PRESCRIPTION DRUG LABEL
Date: 20140603

ACTIVE INGREDIENTS: METAXALONE 800 mg/1 1

PACKAGE LABEL

NDC: 51655-0162-10

MFG: 65162-553-10

Metaxalone, USP

800mg

10 tablets

Rx Only

Dosage: See Package insert

Store below 77 degrees F. (25 degrees C)

Store in a tight, light resistant container (See USP).

Keep out of the reach of children.

Each tablet contains Metaxalone, USP...800mg

Mfg. By Amneal Pharmaceuticals Co. Pvt. Ltd Ahmedabad, India 38220

Repackaged by Northwind Pharmaceuticals, Indianapolis, IN 46256

Lot#:

Exp. Date:

PACKAGE LABEL

NDC: 51655-162-20

MFG: 65162-553-10

Metaxalone Tablets, USP

800 mg

20 Tablets

Rx only

Dosage: See package insert

Store below 77 degrees F.

Store in a tight, light resistant container (See USP) Keep out of the reach of children.

Mfg by: Amneal Pharmaceuticals Co. Pvt. Ltd. Ahmedabad, India 38220

Repackaged by: Northwind Pharmaceuticals, Indianapolis, IN 46256

Lot #:

Exp. Date:

Warnings

Metaxalone may enhance the effects of alcohol and other CNS depressants.

PRECAUTIONS

Metaxalone should be administered with great care to patients with pre-existing liver damage. Serial liver function studies should be performed in these patients.

False-positive Benedict’s tests, due to an unknown reducing substance, have been noted. A glucose-specific test will differentiate findings.

Taking metaxalone with food may enhance general CNS depression; elderly patients may be especially susceptible to this CNS effect. (See CLINICAL PHARMACOLOGY: Pharmacokinetics and PRECAUTIONS: Information for Patients section).

Information for Patients

Metaxalone may impair mental and/or physical abilities required for performance of hazardous tasks, such as operating machinery or driving a motor vehicle, especially when used with alcohol or other CNS depressants.

Drug Interactions

The sedative effects of metaxalone and other CNS depressants (e.g., alcohol, alcohol, benzodiazepines, opioids, tricyclic antidepressants) may be additive. Therefore, caution should be exercised with patients who take more than one of these CNS depressants simultaneously.

Carcinogenesis, Mutagenesis, Impairment of Fertility

The carcinogenic potential of metaxalone has not been determined.

Pregnancy

Reproduction studies in rats have not revealed evidence of impaired fertility or harm to the fetus due to metaxalone. Post marketing experience has not revealed evidence of fetal injury, but such experience cannot exclude the possibility of infrequent or subtle damage to the human fetus. Safe use of metaxalone has not been established with regard to possible adverse effects upon fetal development. Therefore, metaxalone tablets should not be used in women who are or may become pregnant and particularly during early pregnancy unless, in the judgement of the physician, the potential benefits outweigh the possible hazards.

Nursing Mothers

It is not known whether this drug is secreted in human milk. As a general rule, nursing should not be undertaken while a patient is on a drug since many drugs are excreted in human milk.

Pediatric Use

Safety and effectiveness in children 12 years of age and below have not been established.

Adverse Reactions

The most frequent reactions to metaxalone include:

CNS: drowsiness, dizziness, headache, and nervousness or “irritability”;

Digestive: nausea, vomiting, gastrointestinal upset.

Other adverse reactions are:

Immune System: hypersensitivity reaction, rash with or without pruritus;

Hematologic: leukopenia; hemolytic anemia;

Hepatobiliary: jaundice.

Though rare, anaphylactoid reactions have been reported with metaxalone.

Dosage and Administration

The recommended dose for adults and children over 12 years of age is one 800 mg tablet three to four times a day.

Online drug information link

For more information regarding this drug please see the manufacturer's information online at:

Permanent Link:

http://dailymed.nlm.nih.gov/dailymed/lookup.cfm?setid=3aa9dba9-29b0-4520-a0f7-66d19d52c6bc